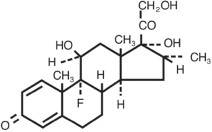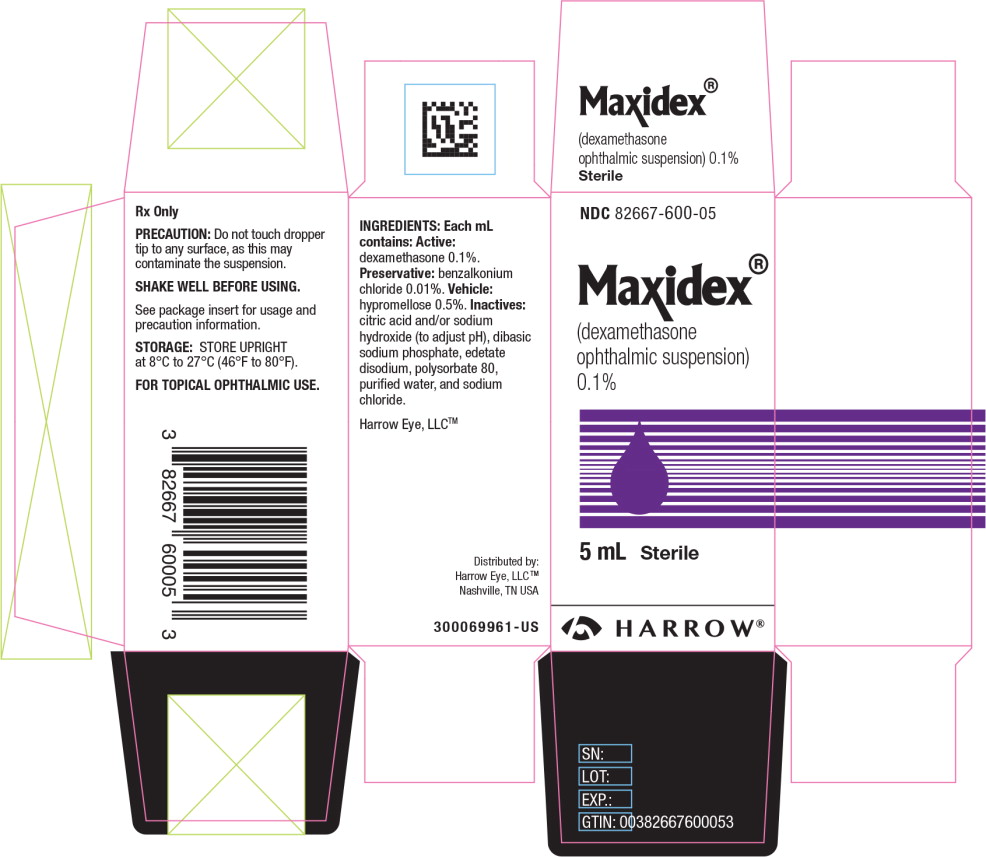 DRUG LABEL: MAXIDEX
NDC: 82667-600 | Form: FOR SUSPENSION
Manufacturer: Harrow Eye, LLC
Category: prescription | Type: HUMAN PRESCRIPTION DRUG LABEL
Date: 20250505

ACTIVE INGREDIENTS: DEXAMETHASONE 1 mg/1 mL
INACTIVE INGREDIENTS: BENZALKONIUM CHLORIDE; HYPROMELLOSE, UNSPECIFIED; SODIUM CHLORIDE; SODIUM PHOSPHATE, DIBASIC, UNSPECIFIED FORM; POLYSORBATE 80; EDETATE DISODIUM; CITRIC ACID MONOHYDRATE; SODIUM HYDROXIDE; WATER

Maxidex®
(dexamethasone ophthalmic suspension) 0.1%
Sterile

DESCRIPTION

MAXIDEX (dexamethasone ophthalmic suspension) 0.1% is an adrenocortical steroid prepared as a sterile topical ophthalmic suspension. The active ingredient is represented by the chemical structure:

Chemical name: Pregna-1,4-diene-3,20-dione,9-fluoro-11,17,21-trihydroxy-16-methyl-,(11β,16α)-.

Each mL of MAXIDEX (dexamethasone ophthalmic suspension) 0.1% contains: Active:dexamethasone 0.1%. Preservative:benzalkonium chloride 0.01%. Vehicle:hypromellose 0.5%. Inactives:citric acid and/or sodium hydroxide (to adjust pH), dibasic sodium phosphate, edetate disodium, polysorbate 80, purified water, and sodium chloride.

CLINICAL PHARMACOLOGY

Dexamethasone suppresses the inflammatory response to a variety of agents and it probably delays or slows healing.

INDICATIONS AND USAGE

Steroid responsive inflammatory conditions of the palpebral and bulbar conjunctiva, cornea, and anterior segment of the globe, such as allergic conjunctivitis, acne rosacea, superficial punctate keratitis, herpes zoster keratitis, iritis, cyclitis, selected infective conjunctivitides when the inherent hazard of steroid use is accepted to obtain an advisable diminution in edema and inflammation; corneal injury from chemical, radiation, or thermal burns, or penetration of foreign bodies.

CONTRAINDICATIONS

Contraindicated in acute, untreated bacterial infections; mycobacterial ocular infections; epithelial herpes simplex (dendritic keratitis); vaccinia, varicella, and most other viral diseases of the cornea and conjunctiva; fungal disease of ocular structures; and in those persons who have shown hypersensitivity to any component of this preparation.

WARNINGS

Prolonged use may result in ocular hypertension and/or glaucoma, with damage to the optic nerve, defects in visual acuity and fields of vision, and posterior subcapsular cataract formation. Prolonged use may suppress the host response and thus increase the hazard of secondary ocular infections. In acute purulent conditions or parasitic infections of the eye, corticosteroids may mask infection or enhance existing infection. In those diseases causing thinning of the cornea or sclera, perforations have been known to occur with the use of topical corticosteroids. If these products are used for 10 days or longer, intraocular pressure (IOP) should be routinely monitored even though it may be difficult in children and uncooperative patients.

Employment of corticosteroid medication in the treatment of herpes simplex other than epithelial herpes simplex keratitis, in which it is contraindicated, requires great caution; periodic slit-lamp microscopy is essential.

PRECAUTIONS

General

FOR TOPICAL OPHTHALMIC USE. The possibility of persistent fungal infections of the cornea should be considered after prolonged corticosteroid dosing.

The initial prescription and renewal of the medication order should be made by a physician only after examination of the patient with the aid of magnification, such as slit lamp biomicroscopy and, where appropriate, fluorescein staining. If signs and symptoms fail to improve after 2 days, the patient should be re-evaluated.

Information for Patients

Do not touch dropper tip to any surface, as this may contaminate the contents. The preservative in MAXIDEX (dexamethasone ophthalmic suspension) 0.1%, benzalkonium chloride, may be absorbed by soft contact lenses. MAXIDEX (dexamethasone ophthalmic suspension) 0.1% should not be administered while wearing soft contact lenses.

Carcinogenesis, Mutagenesis, Impairment of Fertility

Long-term animal studies have not been performed to evaluate the carcinogenic potential or the effect on fertility of MAXIDEX (dexamethasone ophthalmic suspension) 0.1%.

Pregnancy

Dexamethasone has been shown to be teratogenic in mice and rabbits following topical ophthalmic application in multiples of the therapeutic dose. In the mouse, corticosteroids produce fetal resorptions and a specific abnormality, cleft palate. In the rabbit, corticosteroids have produced fetal resorptions and multiple abnormalities involving the head, ears, limbs, palate, etc.

MAXIDEX (dexamethasone ophthalmic suspension) 0.1% should be used during pregnancy only if the potential benefit to the mother justifies the potential risk to the embryo or fetus. There are no adequate or well-controlled studies in pregnant women. However, prolonged or repeated corticoid use during pregnancy has been associated with an increased risk of intra-uterine growth retardation. Infants born of mothers who have received substantial doses of corticosteroids during pregnancy should be observed carefully for signs of hypoadrenalism.

Nursing Mothers

Systemically administered corticosteroids appear in human milk and could suppress growth, interfere with endogenous corticosteroid production, or cause other untoward effects. It is not known whether topical administration of corticosteroids could result in sufficient systemic absorption to produce detectable quantities in human milk. Because many drugs are excreted in human milk, caution should be exercised when MAXIDEX (dexamethasone ophthalmic suspension) 0.1% is administered to a nursing woman.

Pediatric Use

The safety and effectiveness of MAXIDEX have been established in the pediatric patients. Use of MAXIDEX in all pediatric age groups is supported by evidence from adequate and well-controlled studies of MAXIDEX in adults with safety data from additional adequate and well-controlled trials in pediatric patients.

Geriatric Use

No overall differences in safety or effectiveness have been observed between elderly and younger patients.

ADVERSE REACTIONS

Glaucoma with optic nerve damage, visual acuity and field defects; cataract formation; secondary ocular infection following suppression of host response; and perforation of the globe may occur.

Clinical Studies Experience

In clinical studies with MAXIDEX, the most frequently reports adverse reactions were ocular discomfort occurring in approximately 10% of the patients and eye irritation occurring in approximately 1% of the patients. All other adverse reactions from these studies occurred with a frequency less than 1%, including keratitis, conjunctivitis, dry eye, photophobia, blurred vision, eye pruritis, foreign body sensation, increased lacrimation, abnormal ocular sensation, eyelid margin crusting, and ocular hyperemia.

Postmarketing Experience

Additional adverse reactions identified from post-marketing use include corneal erosion, dizziness, eye pain, eyelid ptosis, headache, hypersensitivity reactions, and mydriasis. Frequencies cannot be estimated from the available data.

The following additional adverse reactions have been reported with dexamethasone use:

Cushing's syndrome and adrenal suppression may occur after use of dexamethasone in excess of the listed dosing instructions in predisposed patients, including children and patients treated with CYP3A4 inhibitors.

DOSAGE AND ADMINISTRATION

SHAKE WELL BEFORE USING. One or two drops topically in the conjunctival sac(s). In severe disease, drops may be used hourly, being tapered to discontinuation as the inflammation subsides. In mild disease, drops may be used up to four to six times daily.

Not more than one bottle should be prescribed initially, and the prescription should not be refilled without further evaluation as outlined in PRECAUTIONS above.

HOW SUPPLIED

MAXIDEX®(dexamethasone ophthalmic suspension) 0.1% in plastic dispensers:

5 mL NDC 82667-600-05

STORAGE AND HANDLING

STORAGE:Store upright at 8°C to 27°C (46°F to 80°F).

After opening, MAXIDEX can be used until the expiration date on the bottle.

Distributed by:
Harrow Eye, LLC™
Nashville, TN USA
HARROW®

Revised: December 2024

Principal Display Panel - 5 mL Carton Label

NDC82667-600-05

Maxidex®

(dexamethasone
ophthalmic suspension)
0.1%

5 mL

Sterile

HARROW®